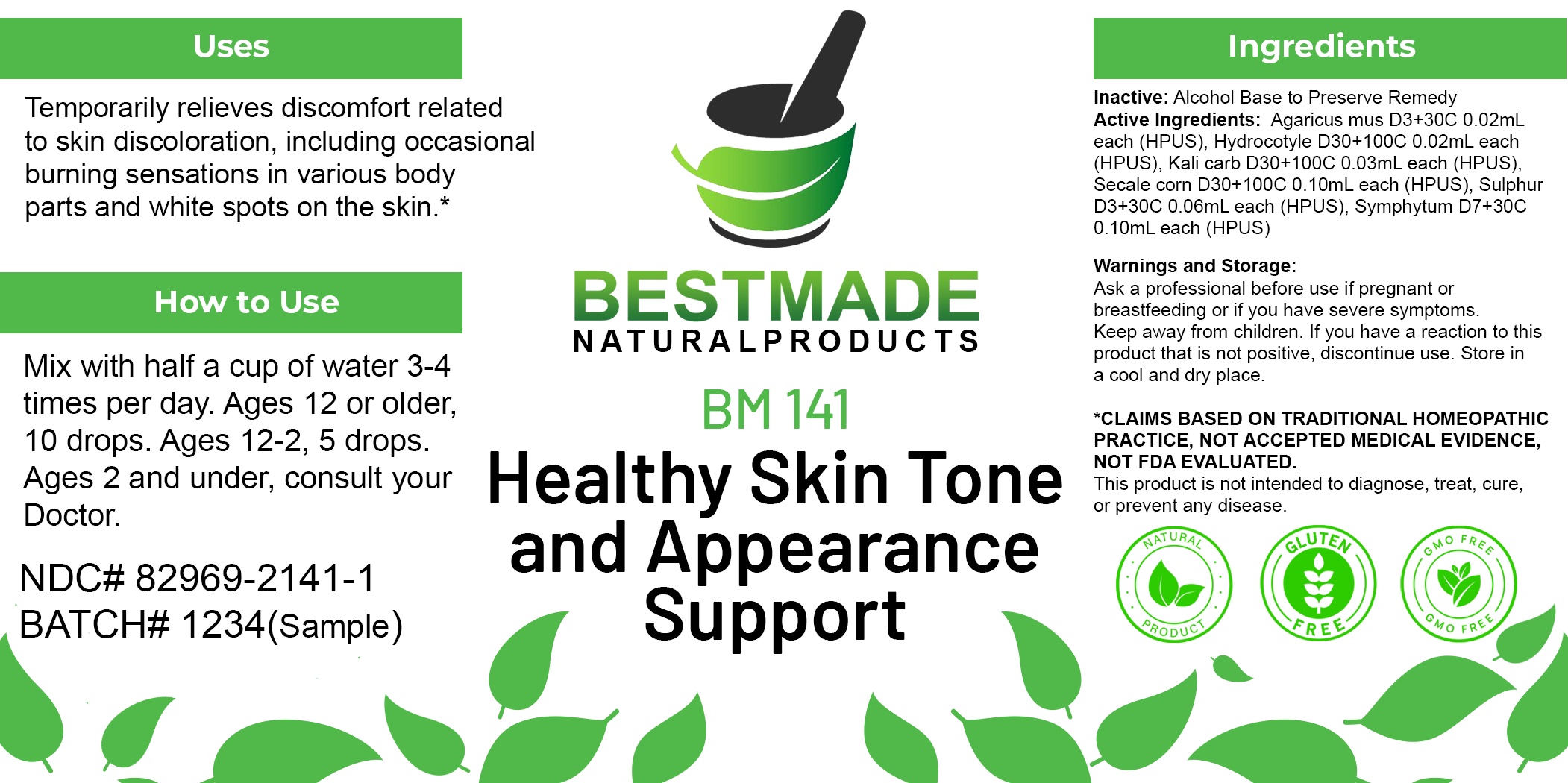 DRUG LABEL: Bestmade Natural Products BM141
NDC: 82969-2141 | Form: LIQUID
Manufacturer: Bestmade Natural Products
Category: homeopathic | Type: HUMAN OTC DRUG LABEL
Date: 20250217

ACTIVE INGREDIENTS: SULFUR 30 [hp_C]/30 [hp_C]; CENTELLA ASIATICA WHOLE 30 [hp_C]/30 [hp_C]; CLAVICEPS PURPUREA SCLEROTIUM 30 [hp_C]/30 [hp_C]; POTASSIUM CARBONATE 30 [hp_C]/30 [hp_C]; COMFREY ROOT 30 [hp_C]/30 [hp_C]; AMANITA MUSCARIA FRUITING BODY 30 [hp_C]/30 [hp_C]
INACTIVE INGREDIENTS: ALCOHOL 30 [hp_C]/30 [hp_C]

BM141

DOSAGE AND ADMINISTRATION

How to Use

Mix with half a cup of water 3-4 times per day. Ages 12 or older, 10 drops. Ages 12-2, 5 drops. Ages 2 and under, consult your Doctor.

Inactive:

Alcohol Base to Preserve Product

ACTIVE INGREDIENTS IN SKIN DISCOLORATION REMEDY

Agaricus mus D3+30C 0.02mL each (HPUS), Hydrocotyle D30+100C 0.02mL each (HPUS), Kali carb D30+100C 0.03mL each (HPUS), Secale corn D30+100C 0.10mL each (HPUS), Sulphur D3+30C 0.06mL each (HPUS), Symphytum D7+30C 0.10mL each (HPUS)

Uses
Temporarily relieves discomfort related to skin discoloration, including occasional burning sensations in various body parts and white spots on the skin.*

Uses
Temporarily relieves discomfort related to skin discoloration, including occasional burning sensations in various body parts and white spots on the skin.*

KEEP OUT OF REACH OF CHILDREN

Warnings and Storage:

Ask a professional before use if pregnant or breastfeeding or if you have severe symptoms.

Keep away from children. If you have a reaction to this product that is not positive, discontinue use. Store in a cool and dry place

*CLAIMS BASED ON TRADITIONAL HOMEOPATHIC PRACTICE, NOT ACCEPTED MEDICAL EVIDENCE NOT FDA EVALUATED.
This product is not intended to diagnose, treat, cure, or prevent any disease.

Warnings and Storage:

Ask a professional before use if pregnant or breastfeeding or if you have severe symptoms.

Keep away from children. If you have a reaction to this product that is not positive, discontinue use. Store in a cool and dry place

*CLAIMS BASED ON TRADITIONAL HOMEOPATHIC PRACTICE, NOT ACCEPTED MEDICAL EVIDENCE NOT FDA EVALUATED.
This product is not intended to diagnose, treat, cure, or prevent any disease.

Entire package label